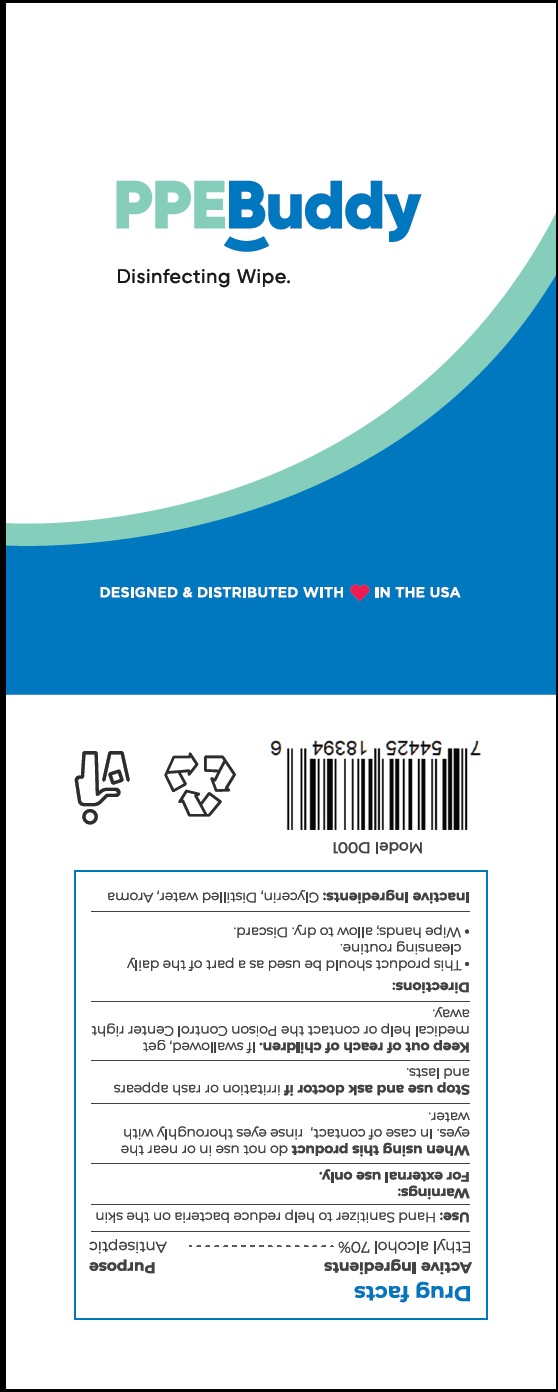 DRUG LABEL: PPE BUDDY
NDC: 80014-002 | Form: CLOTH
Manufacturer: Tecnología en Sachets, S.A. de C.V.
Category: otc | Type: HUMAN OTC DRUG LABEL
Date: 20200814

ACTIVE INGREDIENTS: ALCOHOL 70 mL/100 mL
INACTIVE INGREDIENTS: WATER; DICHROSTACHYS CINEREA WHOLE

Active lngredient

Ethyl alcohol 70%

Purpose

Antiseptic

Use

Hand sanitizer to help reduce bacteria on the skin.

Warnings

For external use only.

When using this product do not use in or near eyes. In case of contact with eyes, rinse eyes thoroughly with water.

Stop use and ask a doctor if irritation or rash appears & last.

Keep out of reach of children. If swallowed, get medical help or contact a Poison Control Center right away.

Directions

This product should be used as a part of the daily cleansing routine.

Wipe hands; allow to dry.Discard.

Inactive ingredients

Glycerin, water (Aqua), Aroma